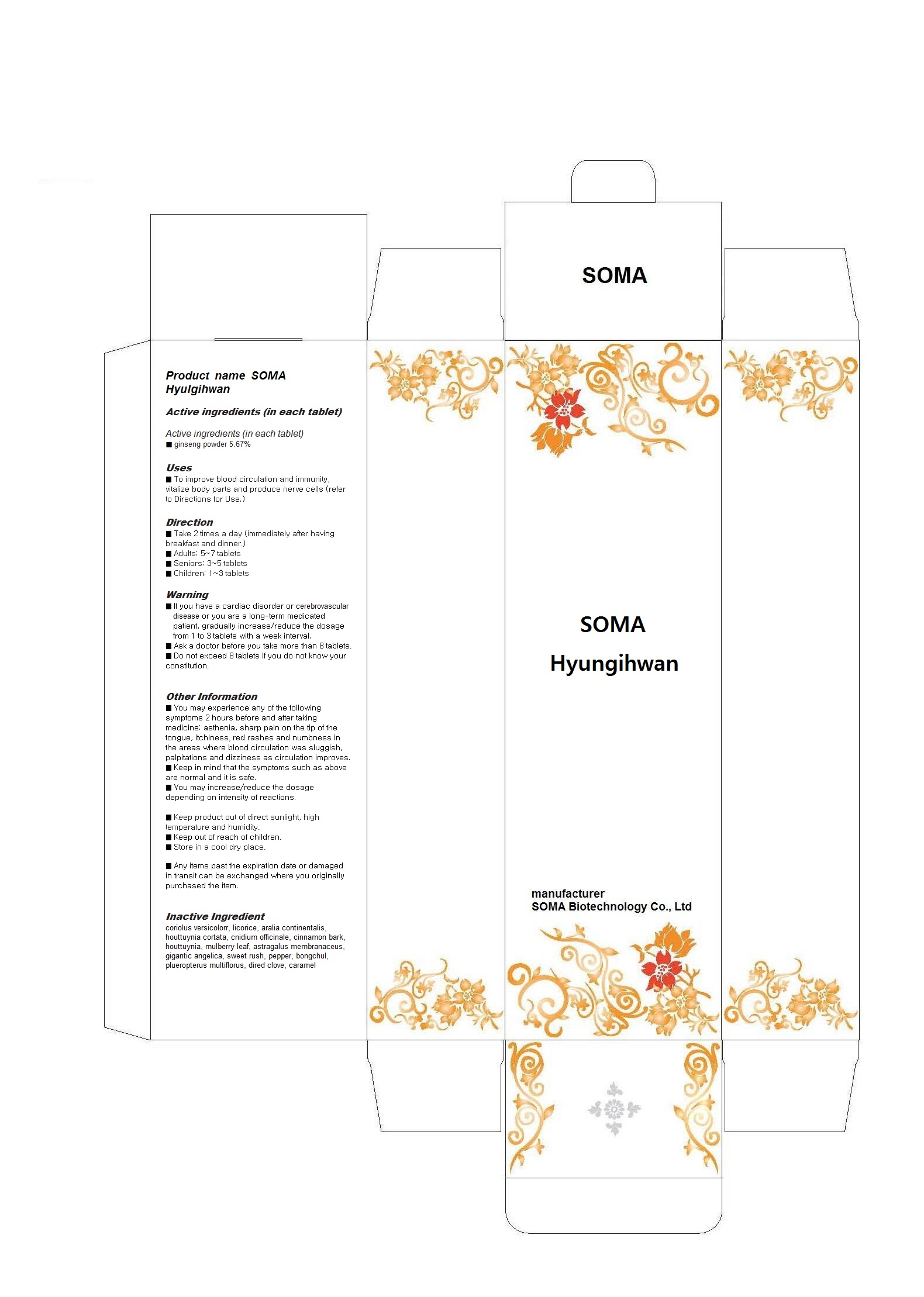 DRUG LABEL: SOMA Hyulgihwan
NDC: 58370-2001 | Form: POWDER
Manufacturer: SOMA Biotechnology Co., Ltd
Category: otc | Type: HUMAN OTC DRUG LABEL
Date: 20130429

ACTIVE INGREDIENTS: ASIAN GINSENG 5.67 g/100 g
INACTIVE INGREDIENTS: TRAMETES VERSICOLOR FRUITING BODY; GLYCYRRHIZA GLABRA; ARALIA CORDATA ROOT; HOUTTUYNIA CORDATA FLOWERING TOP; CNIDIUM OFFICINALE WHOLE; CINNAMON; MORUS AUSTRALIS LEAF; ASTRAGALUS PROPINQUUS ROOT; ANGELICA SINENSIS ROOT; ACORUS GRAMINEUS ROOT; PEPPERS; ZEDOARY; POLYGONUM CUSPIDATUM WHOLE; CLOVE; CARAMEL

Drug Facts

ACTIVE INGREDIENT

red ginseng powder

INACTIVE INGREDIENT

coriolus versicolorr, licorice, aralia continentalis, houttuynia cortata, cnidium officinale, cinnamon bark, houttuynia, mulberry leaf, astragalus membranaceus, gigantic angelica, sweet rush, pepper, bongchul, plueropterus multiflorus, dired clove, caramel

PURPOSE

To improve blood circulation and immunity, vitalize body parts and produce nerve cells

keep out of reach of the children

INDICATIONS AND USAGE

■ Take 2 times a day (immediately after having breakfast and dinner.)
■ Adults: 5~7 tablets
■ Seniors: 3~5 tablets
■ Children: 1~3 tablets

WARNINGS

■ If you have a cardiac disorder or cerebrovascular disease or you are a long-term medicated patient, gradually increase/reduce the dosage from 1 to 3 tablets with a week interval.
■ Ask a doctor before you take more than 8 tablets.
■ Do not exceed 8 tablets if you do not know your constitution

DOSAGE AND ADMINISTRATION

for oral use only